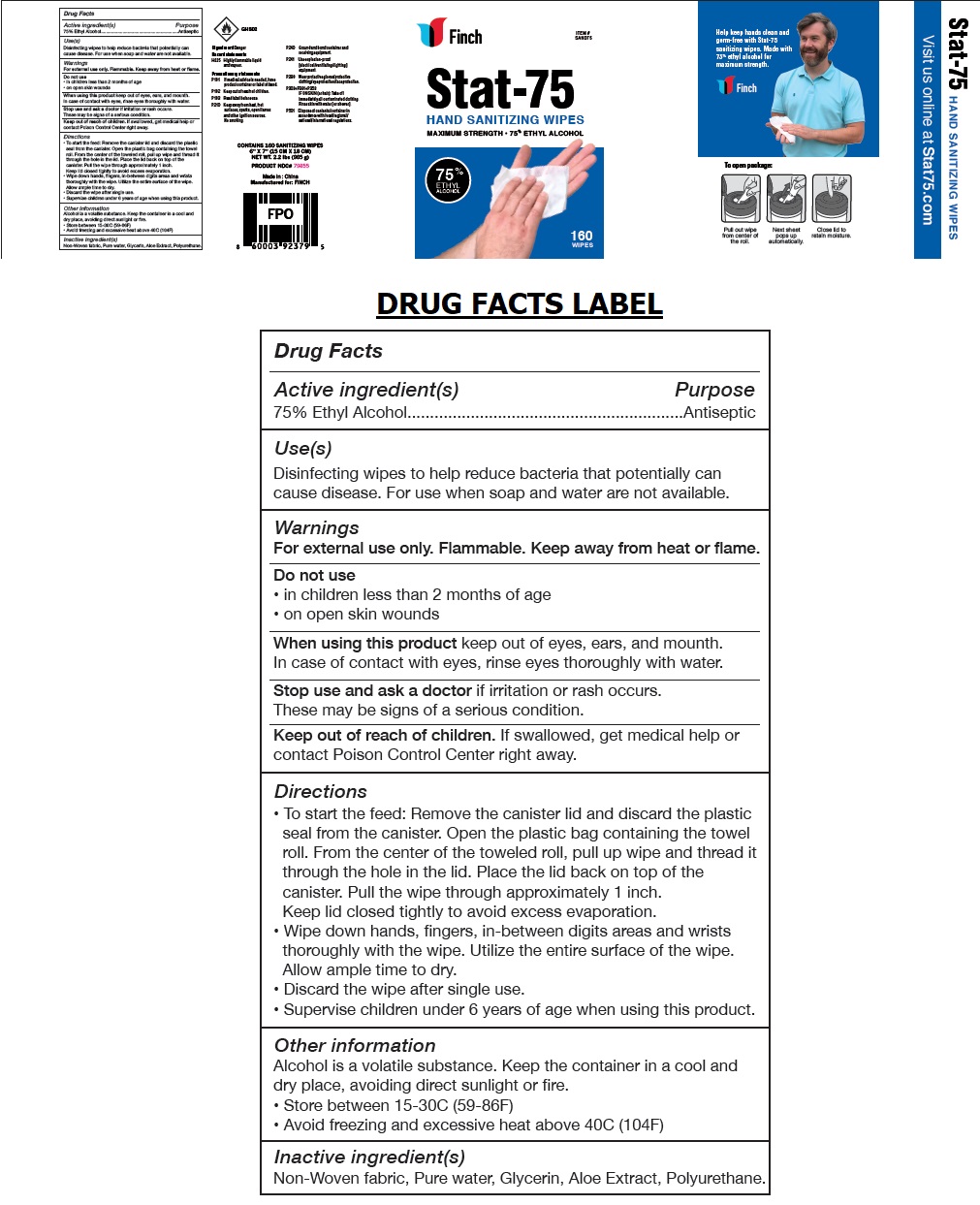 DRUG LABEL: Finch
NDC: 80290-001 | Form: CLOTH
Manufacturer: New Pig Corporation
Category: otc | Type: HUMAN OTC DRUG LABEL
Date: 20200827

ACTIVE INGREDIENTS: ALCOHOL 75 mL/100 mL
INACTIVE INGREDIENTS: WATER; GLYCERIN; ALOE; POLYURETHANE-35 (NOT MORE THAN 500 MPA.S AT 40%)

Finch Stat-75 HAND SANITIZING WIPES

Active ingredient(s)

75% Ethyl Alcohol

Purpose

Antiseptic

Use(s)

Disinfecting wipes to help reduce bacteria that potentially can cause disease. For use when soap and water are not available.

Warnings

For external use only. Flammable. Keep away from heat or flame.

Do not use

• in children less than 2 months of age

• on open skin wounds

When using this product keep out of eyes, ears, and mouth.

In case of contact with eyes, rinse eyes thoroughly with water.

Stop use and ask a doctor if irritation or rash occurs.

These may be signs of a serious condition.

Keep out of reach of children. If swallowed, get medical help or contact a Poison Control Center right away.

Directions

• To start the feed: Remove the canister lid and discard the plastic seal from the canister. Open the

plastic bag containing the towel roll. From the center of the toweled roll, pull up wipe and thread it

through the hole in the lid. Place the lid back on top of the canister. Pull the wipe through

approximately 1 inch.

Keep lid closed tightly to avoid excess evaporation.

• Wipe down hands, fingers, in-between digits areas and wrists thoroughly with the wipe. Utilize the

entire surface of the wipe. Allow ample time to dry.

• Discard the wipe after single use.

• Supervise children under 6 years of age when using this product.

Other information

Alcohol is a volatile substance. Keep the container in a cool and dry place, avoiding direct sunlight or fire.

• Store between 15-30C (59-86F)

• Avoid freezing and excessive heat above 40C (104F)

Inactive ingredient(s)

Non-Woven fabric, Pure water, Glycerin, Aloe Extract, Polyurethane.

MAXIMUM STRENGTH • 75% ETHYL ALCOHOL

Signal word Danger

Hazard statements

H225 Highly flammable liquid and vapour.

Precautionary statements

P101 If medical advice is needed, have product container or label at hand.

P102 Keep out of reach of children.

P103 Read label before use.

P210 Keep away from heat, hot surfaces, sparks, open flames and other ignition sources. No smoking.

P240 Ground and bond container and receiving equipment.

P241 Use explosion-proof [electrical/ventilating/lighting] equipment.

P280 Wear protective gloves/protective clothing/eye protection/face protection.

P303+P361+P353

IF ON SKIN (or hair): Take off immediately all contaminated clothing. Rinse skin with water [or shower].

P501 Dispose of contents/container in accordance with local/regional/national/international regulations.

Made in : China

Manufactured for: FINCH

Help keep hands clean and germ-free with Stat-75 sanitizing wipes. Made with 75% ethyl alcohol for maximum strength.

To open package:

Pull out wipe from center of the roll.

Next sheet pops up automatically.

Close lid to retain moisture.

Visit us online at Stat75.com